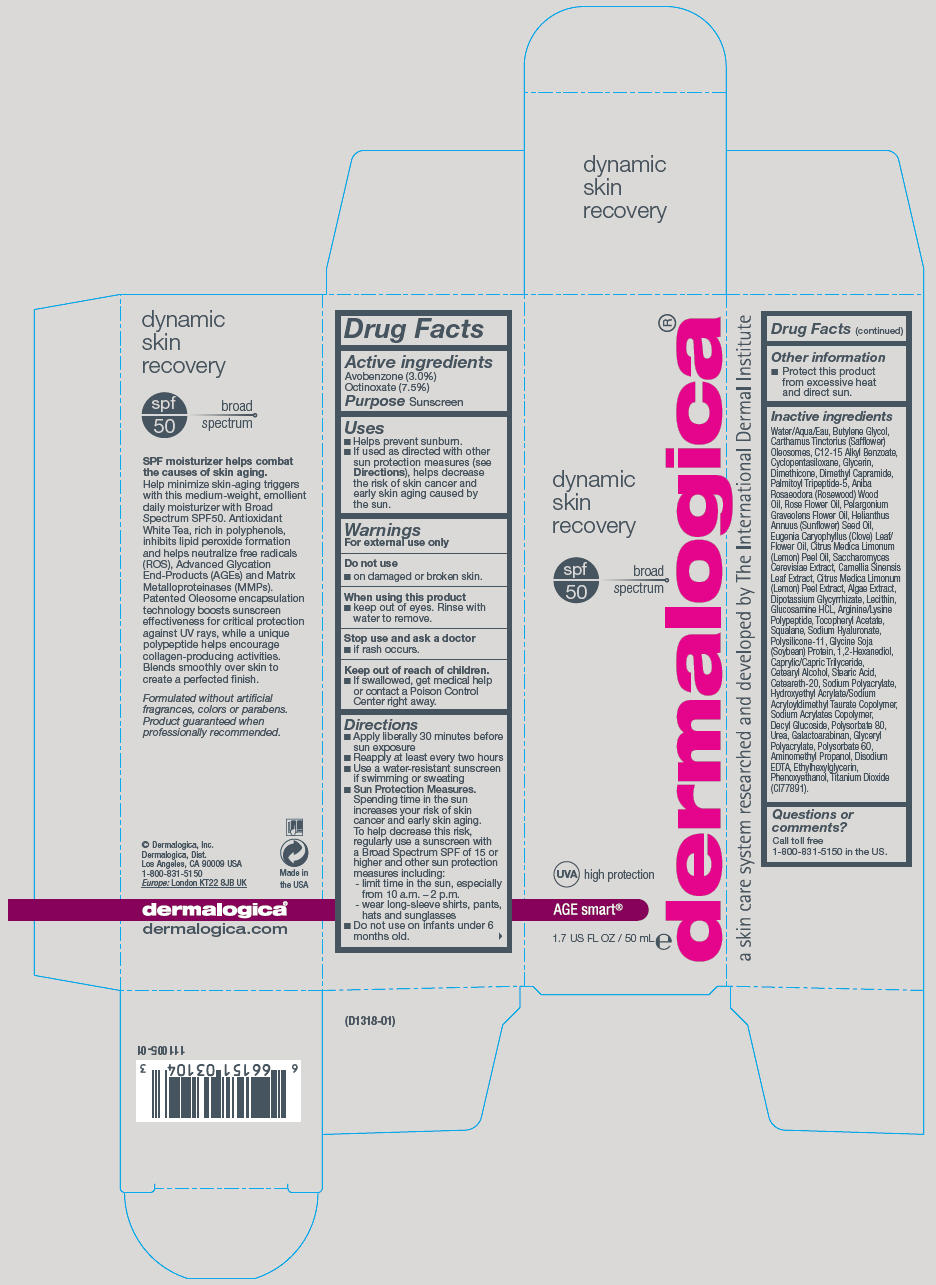 DRUG LABEL: Dynamic Skin Recovery 
NDC: 68479-801 | Form: LOTION
Manufacturer: Dermalogica, Inc.
Category: otc | Type: HUMAN OTC DRUG LABEL
Date: 20171221

ACTIVE INGREDIENTS: Avobenzone 30 mg/1 mL
INACTIVE INGREDIENTS: Water; Butylene Glycol; CARTHAMUS TINCTORIUS SEED OLEOSOMES; ALKYL (C12-15) BENZOATE; CYCLOMETHICONE 5; Glycerin; Dimethicone; Dimethyl Capramide; Palmitoyl Tripeptide-5; ROSEWOOD OIL; Pelargonium Graveolens Flower Oil; SUNFLOWER OIL; LEMON OIL; SACCHAROMYCES CEREVISIAE; GREEN TEA LEAF; LEMON PEEL; GLYCYRRHIZINATE DIPOTASSIUM; GLUCOSAMINE HYDROCHLORIDE; .ALPHA.-TOCOPHEROL ACETATE; Squalane; HYALURONATE SODIUM; DIMETHICONE/VINYL DIMETHICONE CROSSPOLYMER (SOFT PARTICLE); 1,2-Hexanediol; MEDIUM-CHAIN TRIGLYCERIDES; CETOSTEARYL ALCOHOL; Stearic Acid; POLYOXYL 20 CETOSTEARYL ETHER; SODIUM POLYACRYLATE (8000 MW); HYDROXYETHYL ACRYLATE/SODIUM ACRYLOYLDIMETHYL TAURATE COPOLYMER (100000 MPA.S AT 1.5%); Decyl Glucoside; Polysorbate 80; Urea; Galactoarabinan; Polysorbate 60; AMINOMETHYLPROPANOL; EDETATE DISODIUM ANHYDROUS; Ethylhexylglycerin; Phenoxyethanol; Titanium Dioxide

Dynamic Skin Recovery

Drug Facts

Active ingredients

Avobenzone (3.0%)
Octinoxate (7.5%)

Purpose

Sunscreen

Uses

- Helps prevent sunburn.
- If used as directed with other sun protection measures (see Directions), helps decrease the risk of skin cancer and early skin aging caused by the sun.

Warnings

For external use only

Do not use

- on damaged or broken skin.

When using this product

- keep out of eyes. Rinse with water to remove.

Stop use and ask a doctor

- if rash occurs.

Keep out of reach of children.

- If swallowed, get medical help or contact a Poison Control Center right away.

Directions

- Apply liberally 30 minutes before sun exposure
- Reapply at least every two hours
- Use a water-resistant sunscreen if swimming or sweating
- Sun Protection Measures.
  Spending time in the sun increases your risk of skin cancer and early skin aging. To help decrease this risk, regularly use a sunscreen with a Broad Spectrum SPF of 15 or higher and other sun protection measures including:
  - limit time in the sun, especially from 10 a.m. – 2 p.m.
  - wear long-sleeve shirts, pants, hats and sunglasses
- Do not use on infants under 6 months old.

Other information

- Protect this product from excessive heat and direct sun.

Inactive ingredients

Water/Aqua/Eau, Butylene Glycol, Carthamus Tinctorius (Safflower) Oleosomes, C12-15 Alkyl Benzoate, Cyclopentasiloxane, Glycerin, Dimethicone, Dimethyl Capramide, Palmitoyl Tripeptide-5, Aniba Rosaeodora (Rosewood) Wood Oil, Rose Flower Oil, Pelargonium Graveolens Flower Oil, Helianthus Annuus (Sunflower) Seed Oil, Eugenia Caryophyllus (Clove) Leaf/Flower Oil, Citrus Medica Limonum (Lemon) Peel Oil, Saccharomyces Cerevisiae Extract, Camellia Sinensis Leaf Extract, Citrus Medica Limonum (Lemon) Peel Extract, Algae Extract, Dipotassium Glycyrrhizate, Lecithin, Glucosamine HCL, Arginine/Lysine Polypeptide, Tocopheryl Acetate, Squalane, Sodium Hyaluronate, Polysilicone-11, Glycine Soja (Soybean) Protein, 1,2-Hexanediol, Caprylic/Capric Trilyceride, Cetearyl Alcohol, Stearic Acid, Ceteareth-20, Sodium Polyacrylate, Hydroxyethyl Acrylate/Sodium Acryloyldimethyl Taurate Copolymer, Sodium Acrylates Copolymer, Decyl Glucoside, Polysorbate 80, Urea, Galactoarabinan, Glyceryl Polyacrylate, Polysorbate 60, Aminomethyl Propanol, Disodium EDTA, Ethylhexylglycerin, Phenoxyethanol, Titanium Dioxide (CI77891).

Questions or comments?

Call toll free 1-800-831-5150 in the US.

PRINCIPAL DISPLAY PANEL - 50 mL Bottle Carton

dynamic
skin
recovery

spf
50

broad
spectrum

UVA
high protection

AGE smart®

1.7 US FL OZ / 50 mL e

dermalogica®